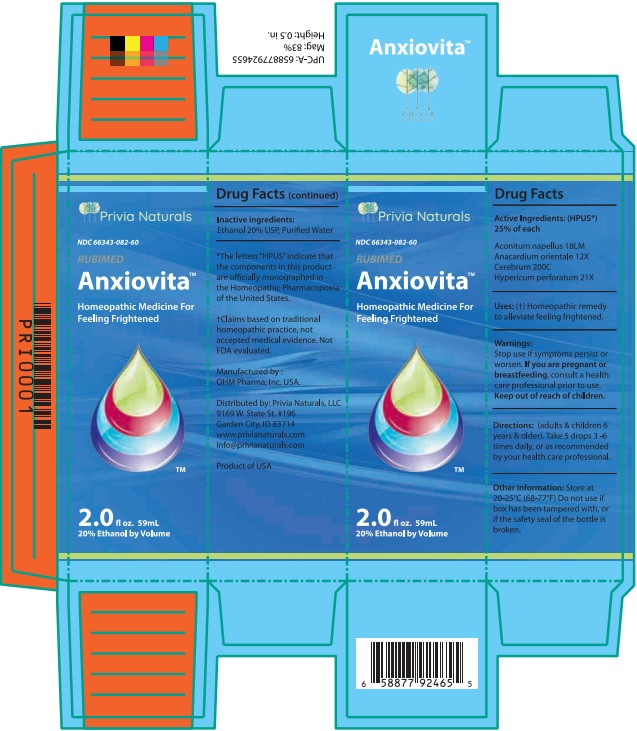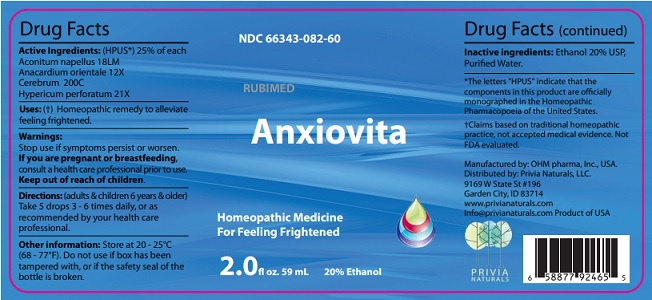 DRUG LABEL: Anxiovita
NDC: 66343-082 | Form: LIQUID
Manufacturer: RUBIMED AG
Category: homeopathic | Type: HUMAN OTC DRUG LABEL
Date: 20241029

ACTIVE INGREDIENTS: ACONITUM NAPELLUS 18 [hp_M]/59 mL; SEMECARPUS ANACARDIUM JUICE 12 [hp_X]/59 mL; SUS SCROFA CEREBRUM 200 [hp_C]/59 mL; HYPERICUM PERFORATUM 21 [hp_X]/59 mL
INACTIVE INGREDIENTS: ALCOHOL; WATER

Anxiovita

Drug Facts

Active ingredients: (HPUS*) 25% of each

Aconitum napellus 18LM

Anacardium orientale 12X

Cerebrum 200C

Hypericum perforatum 21X

*The letters "HPUS" indicate that the components in this product are officially monographed in the Homeopathic Pharmacopoeia of the United States.

Claims based on traditional homeopathic practice, not accepted medical evidence. Not FDA evaluated.

INDICATIONS AND USAGE

Uses: (✝) Homeopathic remedy to alleviate feeling frightened.

Warnings:

Stop use if symptoms persist or worsen.

If you are pregnant or breastfeeding, consult a health care professional prior to use.

Keep out of reach of children.

DOSAGE AND ADMINISTRATION

Directions: (adults & children 6 years & older)

Take 5 drops 3 - 6 times daily, or as recommended by your health care professional.

Other information: Store at 20 - 25°C (68 - 77°F).

Do not use if box has been tampered with, or if the safety seal of

the bottle is broken.

Inactive ingredients: Ethanol 20% USP,

Purified Water.

QUESTIONS

Manufactured by: OHM pharma, Inc, USA.

Distributed by: Privia Naturals, LLC.

9169 W State St # 196

Garden City, ID 83714

www.privianaturals.com

Info@privianaturals.com Product of USA

PACKAGE LABEL

NDC 66343-082-60

RUBIMED

Anxiovita

Homeopathic Medicine

For Feeling Frightened

2.0 fl oz. 59 mL 20% Ethanol

PURPOSE

Homeopathic Medicine For Feeling Frightened.